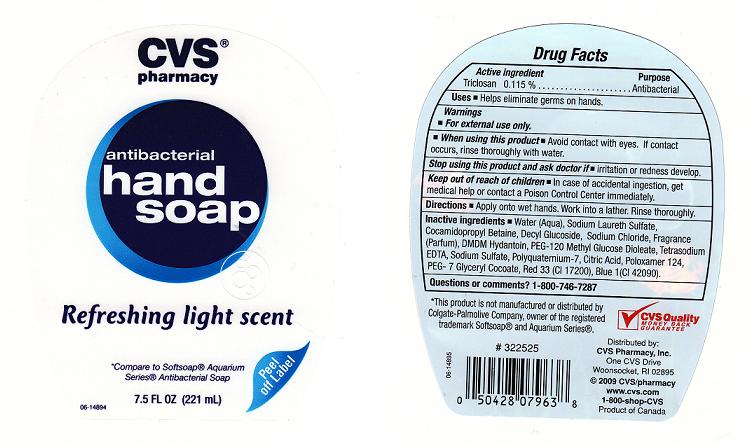 DRUG LABEL: ANTIBACTERIAL HSOAP 
NDC: 59779-720 | Form: LIQUID
Manufacturer: CVS PHARMACY
Category: otc | Type: HUMAN OTC DRUG LABEL
Date: 20110318

ACTIVE INGREDIENTS: TRICLOSAN 0.115 L/100 L
INACTIVE INGREDIENTS: WATER; SODIUM LAURETH SULFATE; COCAMIDOPROPYL BETAINE; LAURYL GLUCOSIDE; SODIUM CHLORIDE; DMDM HYDANTOIN; PEG-120 METHYL GLUCOSE DIOLEATE; EDETATE SODIUM; SODIUM SULFATE; POLYQUATERNIUM-7 (70/30 ACRYLAMIDE/DADMAC; 1600 KD); ANHYDROUS CITRIC ACID; POLOXAMER 124; GLYCERYL COCOATE; D&C RED NO. 33; FD&C BLUE NO. 1

DRUG FACTS

ACTIVE INGREDIENT

TRICLOSAN 0.115%

PURPOSE

ANTIBACTERIAL

USES

HELPS ELIMINATE GERMS ON HANDS.

WARNINGS

FOR EXTERNAL USE ONLY.

WHEN USING THIS PRODUCT

AVOID CONTACT WITH EYES. IF CONTACT OCCURS, RINSE THROUGHLY WITH WATER.

STOP USING THIS PRODUCT AND ASK DOCTOR IF

IRRITATION OR REDNESS DEVELOP.

KEEP OUT OF REACH OF CHILDREN

IN CASE OF ACCIDENTAL INGESTION, GET MEDICAL HELP OR CONTACT A POISON CONTROL CENTER IMMEDIATELY.

DIRECTIONS

APPLY ONTO WET HANDS. WORK INTO LATHER. RINSE THOROUGHLY.

INACTIVE INGREDIENTS

WATER, SODIUM LAURETH SULFATE, COCAMIDOPROPYL BETAINE, DECYL GLUCOSIDE, SODIUM CHLORIDE, FRAGRANCE, DMDM HYDANTOIN, PEG-120 METHYL GLUCOSE DIOLEATE, TETRASODIUM EDTA, SODIUM SULFATE, POLYQUATERNIUM-7, CITRIC ACID, POLOXAMER 124, PEG- 7 GLYCERYL COCOATE, RED 33 (CI 17200), BLUE 1 (CI 42090).

QUESTIONS OR COMMENTS

1-800-748-7287